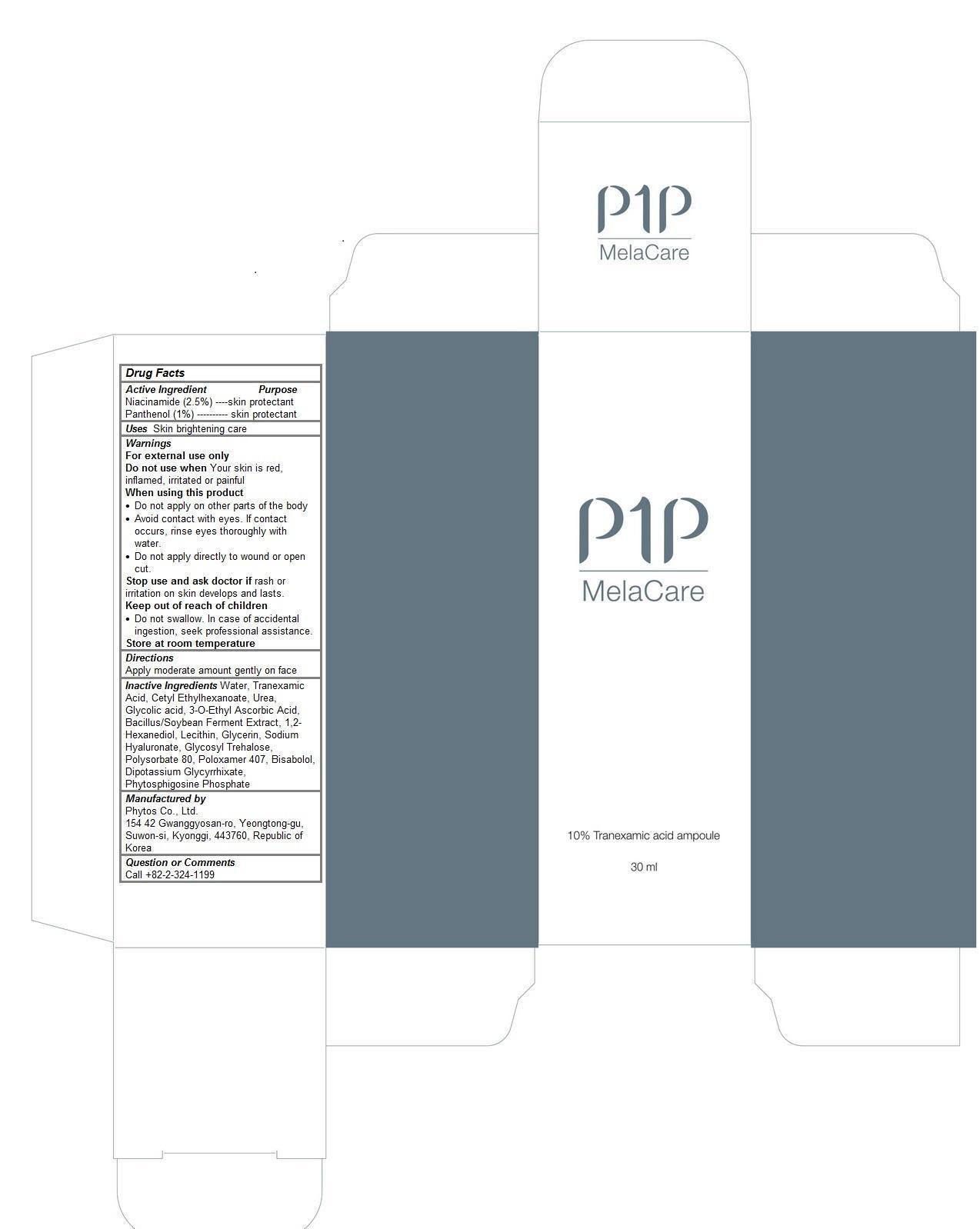 DRUG LABEL: P1P Mela Care
NDC: 69579-101 | Form: LIQUID
Manufacturer: Phytos Co., Ltd.
Category: otc | Type: HUMAN OTC DRUG LABEL
Date: 20150128

ACTIVE INGREDIENTS: NIACINAMIDE 0.025 1/30 mL; PANTHENOL 0.01 1/30 mL
INACTIVE INGREDIENTS: WATER; TRANEXAMIC ACID; CETYL ETHYLHEXANOATE; UREA; GLYCOLIC ACID; 3-O-ETHYL ASCORBIC ACID; 1,2-HEXANEDIOL; GLYCERIN; HYALURONATE SODIUM; POLYSORBATE 80; POLOXAMER 407; LEVOMENOL; GLYCYRRHIZINATE DIPOTASSIUM; EGG PHOSPHOLIPIDS

P1P Mela Care